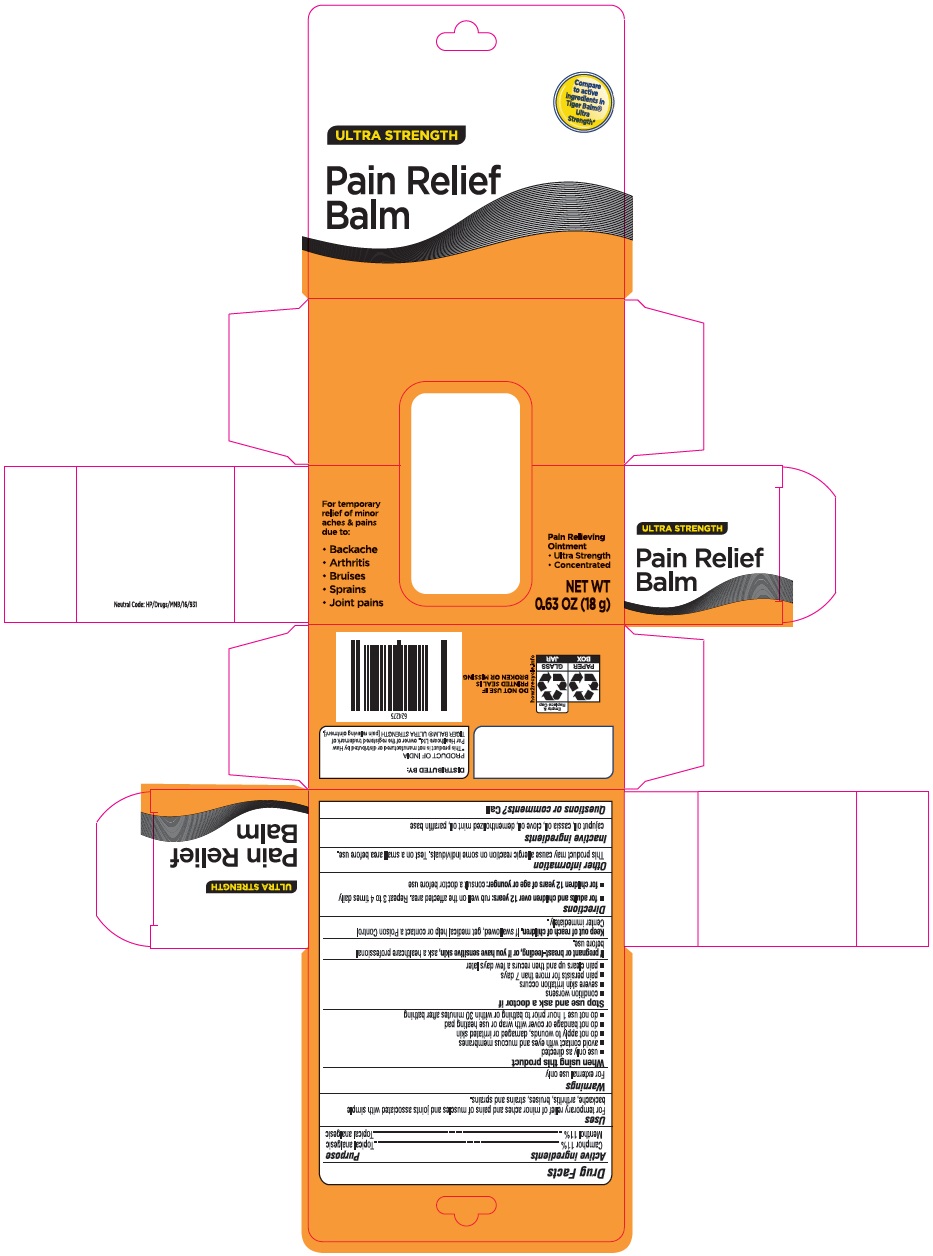 DRUG LABEL: Ultra Strength Pain Relief Balm
NDC: 73492-711 | Form: OINTMENT
Manufacturer: ALAINA HEALTHCARE PRIVATE LIMITED
Category: otc | Type: HUMAN OTC DRUG LABEL
Date: 20251209

ACTIVE INGREDIENTS: CAMPHOR (SYNTHETIC) 110 mg/1 g; MENTHOL 110 mg/1 g
INACTIVE INGREDIENTS: CAJUPUT OIL; CHINESE CINNAMON OIL; CLOVE OIL; PEPPERMINT OIL; PARAFFIN; MINERAL OIL; PETROLATUM

Ultra Strength Pain Relief Balm
Camphor, Menthol ointment

Drug Facts

Active Ingredients

Camphor 11%

Menthol 11%

Purpose

Camphor-Topical Analgesic
Menthol-Topical Analgesic

Uses

For temporary relief of minor aches and pains of muscles and joints associated with simple backache, arthritis, bruises, strains and sprains.

Warnings

For external use only.

When using this product

- Use only as directed.
- avoid contact with eyes and mucous membranes.
- do not apply to wounds, damaged or irritated skin.
- do not bandage or cover with wrap or use heating pad.
- do not use 1 hour prior to bathing or within 30 minutes after bathing.

Stop use and ask a doctor if

- condition worsens.
- severe skin irritation occurs.
- pain persists for more than 7 days.
- pain clears up and then recurs a few days later.

If pregnant or breast-feeding, or if you have sensitive skin,ask a healthcare professional before use.

Keep out of reach of children.If swallowed, get medical help or contact a Poison Control Center immediately.

Directions

- for adults and children over 12 years: rub well on the affected area. Repeat 3 to 4 times daily.
- for children 12 years of age or younger:consult a doctor before use.

Other information

This product may cause allergic reaction on some individuals. Test on a small area before use.

Inactive Ingredients

cajuput oil, cassia oil, clove oil, dementholized mint oil, paraffin base.

*This product is not manufactured or distributed by Haw Par Healthcare Ltd., owner of the registered trademark of Tiger Balm Ultra Strength [pain relieving ointment].

PACKAGE LABEL.PRINCIPAL DISPLAY PANEL

Ultra Strength Pain Relief Balm

For temporary relief of minor aches & pains due to:

- Backache
- Arthritis
- Bruises
- Sprains
- Joint Pains
  Pain Relieving Ointment
- Ultra Strength
- Concentrated

Net wt 0.63 oz (18g)